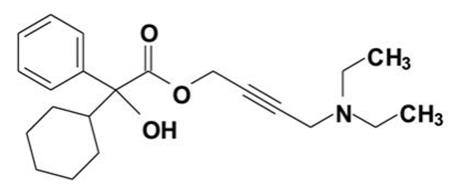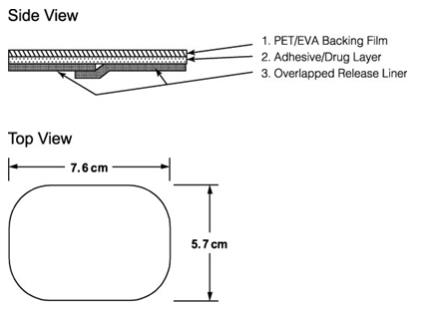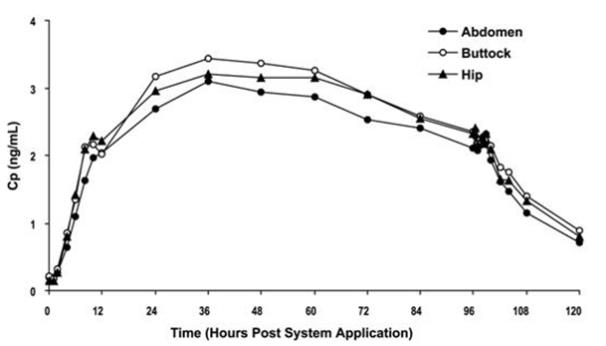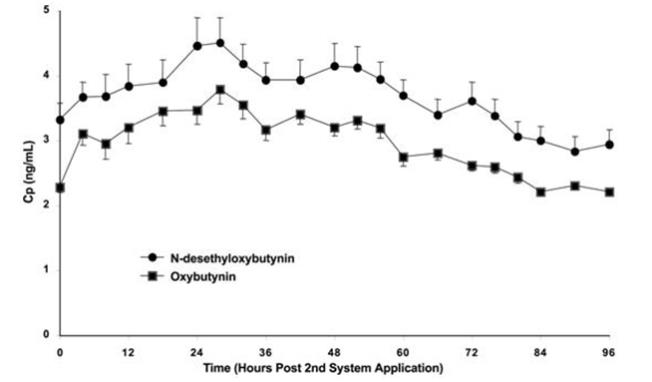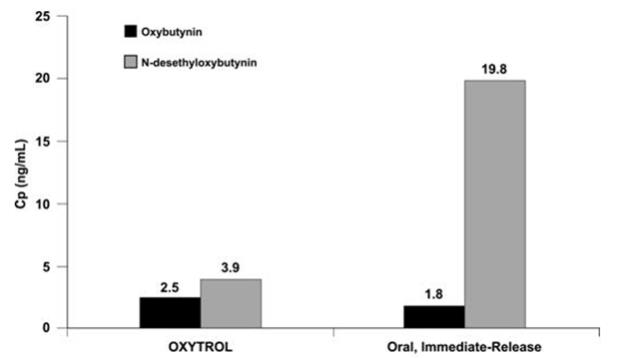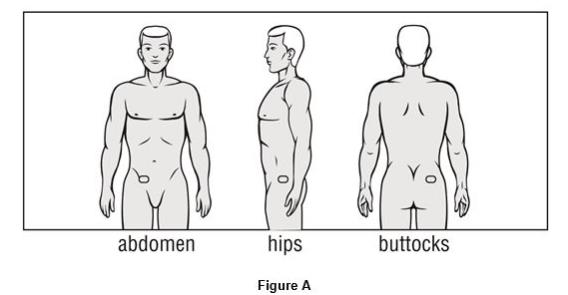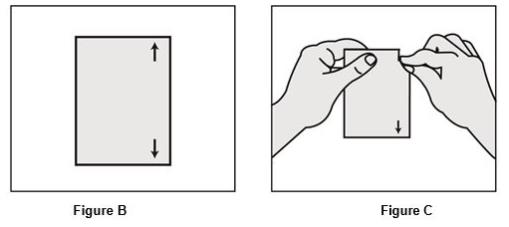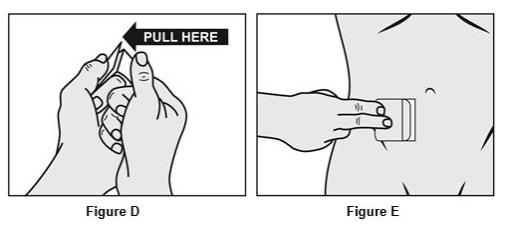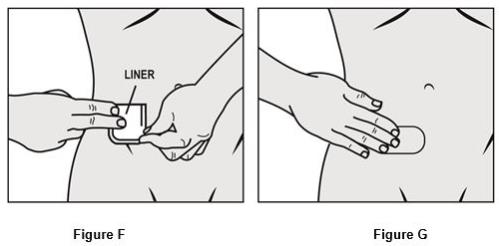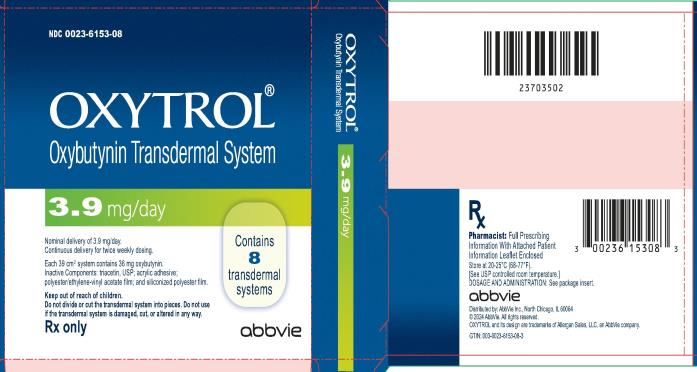 DRUG LABEL: OXYTROL
NDC: 0023-6153 | Form: PATCH
Manufacturer: Allergan, Inc.
Category: prescription | Type: HUMAN PRESCRIPTION DRUG LABEL
Date: 20240529

ACTIVE INGREDIENTS: OXYBUTYNIN 3.9 mg/1 d
INACTIVE INGREDIENTS: TRIACETIN

HIGHLIGHTS OF PRESCRIBING INFORMATION

These highlights do not include all the information needed to use OXYTROL safely and effectively. See full prescribing information for OXYTROL.
OXYTROL® (oxybutynin transdermal system)
Initial U.S. Approval: 1975

RECENT MAJOR CHANGES

Dosage and Administration (2) 5/2024

1 INDICATIONS AND USAGE

OXYTROL is a muscarinic antagonist indicated for the treatment of overactive bladder in men with symptoms of urge urinary incontinence, urgency, and frequency. (1)

2 DOSAGE AND ADMINISTRATION

- Apply OXYTROL transdermal system twice weekly (every 3 to 4 days) to dry, intact skin on the abdomen, hip, or buttocks. (2)
- Select a new application site with each new transdermal system to avoid re-application to the same site within 7 days. (2)
- Do not divide or cut the transdermal system into pieces. Do not use if the transdermal system is damaged.

3 DOSAGE FORMS AND STRENGTHS

Transdermal system: 3.9 mg/day (3)

4 CONTRAINDICATIONS

- Urinary retention (4)
- Gastric retention (4)
- Uncontrolled narrow-angle glaucoma (4)
- Known serious hypersensitivity reaction to OXYTROL, oxybutynin, or to any of the components of OXYTROL (4)

5 WARNINGS AND PRECAUTIONS

- Urinary Retention: Use caution in patients with clinically significant bladder outflow obstruction because of the risk of urinary retention. (5.1)
- Gastrointestinal Disorders: Use caution in patients with gastrointestinal obstructive disorders or decreased intestinal motility because of the risk of gastric retention. Use caution in patients with gastroesophageal reflux and/or those taking drugs that can cause or exacerbate esophagitis. (5.2)
- Central Nervous System Effects: Somnolence has been reported with products containing oxybutynin. Advise patients not to drive or operate heavy machinery until they know how OXYTROL affects them. (5.3)
- Angioedema: Angioedema has been reported with oral oxybutynin use. If symptoms of angioedema occur, discontinue OXYTROL and initiate appropriate therapy. (5.4)
- Skin Hypersensitivity: Discontinue OXYTROL in patients with skin hypersensitivity. (5.5)
- Myasthenia gravis: Avoid use in patients with myasthenia gravis, a disease characterized by decreased cholinergic activity at the neuromuscular junction. (5.6)

6 ADVERSE REACTIONS

The most common adverse reactions (incidence > 5% and > placebo) are application site reactions and dry mouth. (6.1)

To report SUSPECTED ADVERSE REACTIONS, contact AbbVie, Inc. at 1-800-678-1605 or contact the FDA at 1-800-FDA-1088 or www.fda.gov/medwatch.

7 DRUG INTERACTIONS

Other Anticholinergics (muscarinic antagonists): Concomitant use with other anticholinergic agents may increase the frequency and/or severity of dry mouth, constipation, blurred vision, and other anticholinergic pharmacological effects. (7.1)

FULL PRESCRIBING INFORMATION

1 INDICATIONS AND USAGE

OXYTROL is a muscarinic antagonist indicated for the treatment of overactive bladder in men with symptoms of urge urinary incontinence, urgency, and frequency.

2 DOSAGE AND ADMINISTRATION

OXYTROL 3.9 mg/day should be applied to dry, intact skin on the abdomen, hip, or buttock twice weekly (every 3 or 4 days). A new application site should be selected with each new transdermal system to avoid re-application to the same site within 7 days. Do not divide or cut the transdermal system into pieces. Do not use if the transdermal system is damaged.

3 DOSAGE FORMS AND STRENGTHS

Transdermal System: 3.9 mg/day

4 CONTRAINDICATIONS

The use of OXYTROL is contraindicated in the following conditions:

- Urinary retention
- Gastric retention
- Uncontrolled narrow-angle glaucoma
- Known serious hypersensitivity reaction to OXYTROL, oxybutynin, or to any of the components of OXYTROL [see Warnings and Precautions (5.5)].

5 WARNINGS AND PRECAUTIONS

5.1 Urinary Retention

Administer OXYTROL with caution in patients with clinically significant bladder outflow obstruction because of the risk of urinary retention [see Contraindications (4)].

5.2 Risks in Patients with Gastrointestinal Disorders

Administer OXYTROL with caution to patients with gastrointestinal obstructive disorders because of the risk of gastric retention [see Contraindications (4)].

OXYTROL, like other anticholinergic drugs, may decrease gastrointestinal motility and should be used with caution in patients with conditions such as ulcerative colitis or intestinal atony.

OXYTROL should be used with caution in patients who have hiatus hernia/gastroesophageal reflux and/or who are concurrently taking drugs (such as bisphosphonates) that can cause or exacerbate esophagitis.

5.3 Central Nervous System Effects

Products containing oxybutynin are associated with anticholinergic central nervous system (CNS) effects. A variety of CNS anticholinergic effects have been reported, including headache, dizziness, somnolence, confusion and hallucinations [see Adverse Events (6.2)]. Patients should be monitored for signs of anticholinergic CNS effects, particularly after beginning treatment. Advise patients not to drive or operate heavy machinery until they know how OXYTROL affects them. If a patient experiences anticholinergic CNS effects, drug discontinuation should be considered.

5.4 Angioedema

Angioedema requiring hospitalization and emergency medical treatment has occurred with the first or subsequent doses of oral oxybutynin. In the event of angioedema, OXYTROL should be discontinued and appropriate therapy promptly provided.

5.5 Skin Hypersensitivity

Patients who develop skin hypersensitivity to OXYTROL should discontinue drug treatment.

5.6 Exacerbation of Symptoms of Myasthenia Gravis

Avoid use of OXYTROL in patients with myasthenia gravis, a disease characterized by decreased cholinergic activity at the neuromuscular junction. If experiencing exacerbation of symptoms of myasthenia gravis, oxybutynin-containing product should be discontinued and appropriate therapy promptly provided.

6 ADVERSE REACTIONS

6.1 Clinical Trials Experience

Because clinical trials are conducted under widely varying conditions, adverse reaction rates observed in the clinical trials of a drug cannot be directly compared to rates in the clinical trials of another drug and may not reflect the rates observed in clinical practice.

The safety of OXYTROL was evaluated in a total of 417 patients who participated in two clinical efficacy and safety studies and an open-label extension. Additional safety information was collected in earlier phase trials. In the two pivotal studies, a total of 246 patients received OXYTROL during the 12-week treatment periods. A total of 411 patients entered the open-label extension and of those, 65 patients and 52 patients received OXYTROL for at least 24 weeks and at least 36 weeks, respectively.

No deaths were reported during treatment. No serious adverse events related to treatment were reported.

Adverse reactions reported in the pivotal trials are summarized in Tables 1 and 2 below.

Table 1: Number (%) of adverse reactions occurring in ≥ 2% of OXYTROL-treated patients and greater in the OXYTROL group than in the placebo group (Study 1).
Adverse Reaction | Placebo (N = 132) |  | OXYTROL (3.9 mg/day) (N = 125)
 | N | % | N | %
Application site pruritus | 8 | 6.1% | 21 | 16.8%
Dry mouth | 11 | 8.3% | 12 | 9.6%
Application site erythema | 3 | 2.3% | 7 | 5.6%
Application site vesicles | 0 | 0.0% | 4 | 3.2%
Diarrhea | 3 | 2.3% | 4 | 3.2%
Dysuria | 0 | 0.0% | 3 | 2.4%

Table 2: Number (%) of adverse reactions occurring in ≥ 2% of OXYTROL-treated patients and greater in the OXYTROL group than in the placebo group (Study 2).
Adverse Reaction | Placebo (N = 117) |  | OXYTROL (3.9 mg/day) (N = 121)
 | N | % | N | %
Application site pruritus | 5 | 4.3% | 17 | 14.0%
Application site erythema | 2 | 1.7% | 10 | 8.3%
Dry mouth | 2 | 1.7% | 5 | 4.1%
Constipation | 0 | 0.0% | 4 | 3.3%
Application site rash | 1 | 0.9% | 4 | 3.3%
Application site macules | 0 | 0.0% | 3 | 2.5%
Abnormal vision | 0 | 0.0% | 3 | 2.5%

Most adverse reactions were described as mild or moderate in intensity. Severe application site reactions were reported by 6.4% of OXYTROL-treated patients in Study 1 and by 5.0% of OXYTROL-treated patients in Study 2.

Adverse reactions that resulted in discontinuation were reported by 11.2% of OXYTROL-treated patients in Study 1 and 10.7% of OXYTROL-treated patients in Study 2. Most of these discontinuations were due to application site reaction. In the two pivotal studies, no patient discontinued OXYTROL treatment due to dry mouth.

In the open-label extension, the most common treatment-related adverse reactions were: application site pruritus, application site erythema, and dry mouth.

6.2 Postmarketing Experience

The following adverse reactions have been identified during post approval use of OXYTROL. Because these reactions are reported voluntarily from a population of uncertain size, it is not always possible to reliably estimate their frequency or establish a causal relationship to drug exposure.

Nervous System Disorders: Memory impairment, dizziness, somnolence, confusion

Psychiatric Disorders: Delirium, hallucinations

7 DRUG INTERACTIONS

No specific drug-drug interaction studies have been performed with OXYTROL.

7.1 Other Anticholinergics

The concomitant use of OXYTROL with other anticholinergic drugs, or with other agents that produce dry mouth, constipation, somnolence, and/or other anticholinergic-like effects may increase the frequency and/or severity of such effects. Anticholinergic agents may potentially alter the absorption of some concomitantly administered drugs due to anticholinergic effects on gastrointestinal motility.

7.2 Cytochrome P450 Inhibitors

Pharmacokinetic studies have not been performed with patients concomitantly receiving cytochrome P450 enzyme inhibitors, such as antimycotic agents (e.g., ketoconazole, itraconazole, and miconazole) or macrolide antibiotics (e.g., erythromycin and clarithromycin).

8 USE IN SPECIFIC POPULATIONS

8.1 Pregnancy

Risk Summary

There are no studies with topical or oral oxybutynin use in pregnant women to inform a drug associated risk for birth defects or miscarriage. No adverse developmental outcomes were observed in animal reproduction studies when oxybutynin chloride was administered to pregnant rats and rabbits during organogenesis at approximately 50 and 1 times, respectively, the maximum human dose based on body surface area (see Data).

In the U.S. general population, the estimated background risk of major birth defects and miscarriage in clinically recognized pregnancies is 2-4% and 15-20% respectively.

Data

Animal Data

Subcutaneous administration of oxybutynin chloride to rats at doses up to 25 mg/kg (approximately 50 times the human exposure based on surface area) and to rabbits at doses up to 0.4 mg/kg (approximately 1 times the human exposure based on body surface area) throughout the period of organogenesis revealed no evidence of harm to the fetus.

8.2 Lactation

Risk Summary

There is no information on the presence of oxybutynin in human milk, the effects on the breastfed child, or the effects on milk production. The developmental and health benefits of breastfeeding should be considered along with the mother’s clinical need for OXYTROL and any potential adverse effects on the breastfed child from OXYTROL or from the underlying maternal condition.

8.4 Pediatric Use

The safety and efficacy of OXYTROL in pediatric patients have not been established.

8.5 Geriatric Use

Forty-nine percent of OXYTROL-treated patients in the clinical studies were at least 65 years of age. No overall differences in safety or effectiveness were observed between these patients and younger patients, and other reported clinical experience has not identified differences in response between elderly and younger patients, but greater sensitivity of some older individuals cannot be ruled out [see Clinical Pharmacology (12.3)].

10 OVERDOSAGE

The plasma concentration of oxybutynin declines within 1 to 2 hours after removal of transdermal system(s). Patients should be monitored until symptoms resolve. Overdosage with oxybutynin has been associated with anticholinergic effects including CNS excitation, flushing, fever, dehydration, cardiac arrhythmia, vomiting, and urinary retention. Ingestion of 100 mg oral oxybutynin chloride in association with alcohol has been reported in a 13 year old boy who experienced memory loss, and in a 34 year old woman who developed stupor, followed by disorientation and agitation on awakening, dilated pupils, dry skin, cardiac arrhythmia, and retention of urine. Both patients recovered fully with treatment directed at their symptoms.

11 DESCRIPTION

OXYTROL (oxybutynin transdermal system) is designed to deliver oxybutynin over a 3- to 4-day interval after application to intact skin. OXYTROL is available as a 39 cm^2 transdermal system containing 36 mg of oxybutynin. OXYTROL has a nominal in vivo delivery rate of 3.9 mg oxybutynin per day through skin of average permeability (inter-individual variation in skin permeability is approximately 20%).

Oxybutynin is an antispasmodic, anticholinergic agent. Oxybutynin is administered as a racemate of R- and S-isomers. Chemically, oxybutynin is d, l (racemic) 4-diethylamino-2-butynyl phenylcyclohexylglycolate. The empirical formula of oxybutynin is C22H31NO3. Its structural formula is:

Oxybutynin is a white powder with a molecular weight of 357. It is soluble in alcohol, but relatively insoluble in water.

OXYTROL is a matrix-type transdermal system composed of three layers as illustrated in Figure 1. Layer 1 (Backing Film) is a thin flexible polyester/ethylene-vinyl acetate film that provides the matrix transdermal system with occlusivity and physical integrity and protects the adhesive/drug layer. Layer 2 (Adhesive/Drug Layer) is a cast film of acrylic adhesive containing oxybutynin and triacetin, USP. Layer 3 (Release Liner) is two overlapped siliconized polyester strips that are peeled off and discarded by the patient prior to applying the matrix transdermal system.

Figure 1: Side and top views of the OXYTROL transdermal system.
(Not to scale)

12 CLINICAL PHARMACOLOGY

12.1 Mechanism of Action

The free base form of oxybutynin is pharmacologically equivalent to oxybutynin hydrochloride. Oxybutynin acts as a competitive antagonist of acetylcholine at postganglionic muscarinic receptors, resulting in relaxation of bladder smooth muscle. In patients with conditions characterized by involuntary detrusor contractions, cystometric studies have demonstrated that oxybutynin increases maximum urinary bladder capacity and increases the volume to first detrusor contraction.

Oxybutynin is a racemic (50:50) mixture of R- and S-isomers. Antimuscarinic activity resides predominantly in the R-isomer. The active metabolite, N-desethyloxybutynin, has pharmacological activity on the human detrusor muscle that is similar to that of oxybutynin in in vitro studies.

12.3 Pharmacokinetics

Absorption

Oxybutynin is transported across intact skin and into the systemic circulation by passive diffusion across the stratum corneum. The average daily dose of oxybutynin absorbed from the 39 cm^2 OXYTROL transdermal system is 3.9 mg. The average (SD) nominal dose, 0.10 (0.02) mg oxybutynin per cm^2 surface area, was obtained from analysis of residual oxybutynin content of transdermal systems worn over a continuous 4-day period during 303 separate occasions in 76 healthy volunteers. Following application of the first OXYTROL 3.9 mg/day transdermal system, oxybutynin plasma concentrations increase for approximately 24 to 48 hours, reaching average maximum concentrations of 3 to 4 ng/mL. Thereafter, steady concentrations are maintained for up to 96 hours. Absorption of oxybutynin is bioequivalent when OXYTROL is applied to the abdomen, buttocks, or hip. Average plasma concentrations measured during a randomized, crossover study of the three recommended application sites in 24 healthy men and women are shown in Figure 2.

Figure 2: Average plasma oxybutynin concentrations (Cp) in 24 healthy male and female volunteers during single-dose application of OXYTROL 3.9 mg/day to the abdomen, buttock, and hip (Transdermal System removal at 96 hours).

Steady-state conditions are reached during the second OXYTROL application. Average steady-state plasma concentrations were 3.1 ng/mL for oxybutynin and 3.8 ng/mL for N-desethyloxybutynin (Figure 3). Table 3 provides a summary of pharmacokinetic parameters of oxybutynin in healthy volunteers after single and multiple applications of OXYTROL.

Figure 3: Average (SEM) steady-state oxybutynin and N-desethyloxybutynin plasma concentrations (Cp) measured in 13 healthy volunteers following the second transdermal system application in a multiple-dose, randomized, crossover study.

Table 3: Mean (SD) oxybutynin pharmacokinetic parameters from single and multiple dose studies in healthy men and women volunteers after application of OXYTROL on the abdomen.
Dosing | Oxybutynin
 | Cmax (SD) (ng/mL) | Tmax^1 (hr) | Cavg (SD) (ng/mL) | AUC (SD) (ng/mLxh)
Single | 3.0 (0.8) | 48 | - | 245 (59)^2
 | 3.4 (1.1) | 36 | - | 279 (99)^2
Multiple | 6.6 (2.4) | 10 | 4.2 (1.1) | 408 (108)^3
 | 4.2 (1.0) | 28 | 3.1 (0.7) | 259 (57)^4
^1Tmax given as median
^2AUCinf
^3AUC0-96
^4AUC0-84

Distribution

Oxybutynin is widely distributed in body tissues following systemic absorption. The volume of distribution was estimated to be 193 L after intravenous administration of 5 mg oxybutynin chloride.

Metabolism

Oxybutynin is metabolized primarily by the cytochrome P450 enzyme systems, particularly CYP3A4, found mostly in the liver and gut wall. Metabolites include phenylcyclohexylglycolic acid, which is pharmacologically inactive, and N-desethyloxybutynin, which is pharmacologically active.

After oral administration of oxybutynin, pre-systemic first-pass metabolism results in an oral bioavailability of approximately 6% and higher plasma concentration of the N-desethyl metabolite compared to oxybutynin (see Figure 4). The plasma concentration area under the time-concentration curve (AUC) ratio of N-desethyl metabolite to parent compound following a single 5 mg oral dose of oxybutynin chloride was 11.9:1.

Transdermal administration of oxybutynin bypasses first-pass gastrointestinal and hepatic metabolism, reducing the formation of the N-desethyl metabolite (see Figure 4). Only small amounts of CYP3A4 are found in skin, limiting pre-systemic metabolism during transdermal absorption. The resulting plasma concentration AUC ratio of N-desethyl metabolite to parent compound following multiple OXYTROL applications was 1.3:1.

Figure 4: Average plasma concentrations (Cp) measured after a single, 96-hour application of the OXYTROL 3.9 mg/day transdermal system (AUCinf/96) and a single, 5 mg, oral immediate-release dose of oxybutynin chloride (AUCinf/8) in 16 healthy male and female volunteers.

Following intravenous administration, the elimination half-life of oxybutynin is approximately 2 hours. Following removal of OXYTROL, plasma concentrations of oxybutynin and N-desethyloxybutynin decline with an apparent half-life of approximately 7 to 8 hours.

Excretion

Oxybutynin is extensively metabolized by the liver, with less than 0.1% of the administered dose excreted unchanged in the urine. Also, less than 0.1% of the administered dose is excreted as the metabolite N-desethyloxybutynin.

Specific Populations:

Geriatric: The pharmacokinetics of oxybutynin and N-desethyloxybutynin were similar in older and younger patients.

Pediatric: The pharmacokinetics of oxybutynin and N-desethyloxybutynin were not evaluated in individuals younger than 18 years of age.

Gender: There were no significant differences in the pharmacokinetics of oxybutynin in healthy male and female volunteers following application of OXYTROL.

Race: Available data suggest that there are no significant differences in the pharmacokinetics of oxybutynin based on race in healthy volunteers following administration of OXYTROL. Japanese volunteers demonstrated a somewhat lower metabolism of oxybutynin to N-desethyloxybutynin compared to Caucasian volunteers.

13 NONCLINICAL TOXICOLOGY

13.1 Carcinogenesis, Mutagenesis, Impairment of Fertility

A 24-month study in rats at dosages of oxybutynin chloride of 20, 80 and 160 mg/kg showed no evidence of carcinogenicity. These doses are approximately 6, 25 and 50 times the maximum exposure in humans taking an oral dose based on body surface area.

Oxybutynin chloride showed no increase of mutagenic activity when tested in Schizosaccharomyces pompholiciformis, Saccharomyces cerevisiae, and Salmonella typhimurium test systems. Reproduction studies with oxybutynin chloride in the mouse, rat, hamster, and rabbit showed no definite evidence of impaired fertility.

14 CLINICAL STUDIES

The efficacy and safety of OXYTROL were evaluated in patients with urge urinary incontinence in two controlled studies and one open-label extension. Study 1 was a placebo controlled study, comparing the safety and efficacy of OXYTROL at dose levels of 1.3, 2.6, and 3.9 mg/day to placebo in 520 patients. Open-label treatment was available for patients completing the study. Study 2 was a study comparing the safety and efficacy of OXYTROL 3.9 mg/day versus active and placebo controls in 361 patients.

Study 1 was a randomized, double-blind, placebo-controlled, parallel group study of three dose levels of OXYTROL conducted in 520 patients. The 12-week double-blind treatment included an OXYTROL dose of 3.9 mg/day or matching placebo. An open-label, dose titration treatment extension allowed continued treatment for up to an additional 40 weeks for patients completing the double-blind period. The majority of patients were Caucasian (91%) and female (92%) with a mean age of 61 years (range, 20 to 88 years). Entry criteria required that patients have urge or mixed incontinence (with a predominance of urge), urge incontinence episodes of ≥ 10 per week, and ≥ 8 micturitions per day. The patient’s medical history and a urinary diary during the treatment-free baseline period confirmed the diagnosis of urge incontinence. Approximately 80% of patients had no prior pharmacological treatment for incontinence. Changes in weekly incontinence episodes, urinary frequency, and urinary void volume between placebo and active treatment groups are summarized in Table 4.

Table 4: Mean and median change from baseline to end of treatment (Week 12 or last observation carried forward) in incontinence episodes, urinary frequency, and urinary void volume in patients treated with OXYTROL 3.9 mg/day or placebo for 12 weeks (Study 1).
Parameter | Placebo (N = 127) |  | OXYTROL 3.9 mg/day (N = 120)
 | Mean (SD) | Median | Mean (SD) | Median
Weekly Incontinence Episodes
Baseline | 37.7 (24.0) | 30 | 34.3 (18.2) | 31
Reduction | 19.2 (21.4) | 15 | 21.0 (17.1) | 19
p value vs. placebo | - |  | 0.0265*
Daily Urinary Frequency
Baseline | 12.3 (3.5) | 11 | 11.8 (3.1) | 11
Reduction | 1.6 (3.0) | 1 | 2.2 (2.5) | 2
p value vs. placebo | - |  | 0.0313*
Urinary Void Volume (mL)
Baseline | 175.9 (69.5) | 166.5 | 171.6 (65.1) | 168
Increase | 10.5 (56.9) | 5.5 | 31.6 (65.6) | 26
p value vs. placebo | - |  | 0.0009**
*Comparison significant if p < 0.05
**Comparison significant if p ≤ 0.0167

Study 2 was a randomized, double-blind, study of OXYTROL 3.9 mg/day versus active and placebo controls conducted in 361 patients. The 12-week double-blind treatment included an OXYTROL dose of 3.9 mg/day, an active comparator, and placebo. The majority of patients were Caucasian (95%) and female (93%) with a mean age of 64 years (range, 18 to 89 years). Entry criteria required that all patients have urge or mixed incontinence (with a predominance of urge) and had achieved a beneficial response from the anticholinergic treatment they were using at the time of study entry. The average duration of prior pharmacological treatment was greater than 2 years. The patient’s medical history and a urinary diary during the treatment-free baseline period confirmed the diagnosis of urge incontinence. Changes in daily incontinence episodes, urinary frequency, and urinary void volume between placebo and active treatment groups are summarized in Table 5.

Table 5: Mean and median change from baseline to end of treatment (Week 12 or last observation carried forward) in incontinence episodes, urinary frequency, and urinary void volume in patients treated with OXYTROL 3.9 mg/day or placebo for 12 weeks (Study 2).
Parameter | Placebo (N = 117) |  | OXYTROL 3.9 mg/day (N = 121)
 | Mean (SD) | Median | Mean (SD) | Median
Daily Incontinence Episodes
Baseline | 5.0 (3.2) | 4 | 4.7 (2.9) | 4
Reduction | 2.1 (3.0) | 2 | 2.9 (3.0) | 3
p value vs. placebo | - |  | 0.0137*
Daily Urinary Frequency
Baseline | 12.3 (3.3) | 12 | 12.4 (2.9) | 12
Reduction | 1.4 (2.7) | 1 | 1.9 (2.7) | 2
p value vs. placebo | - |  | 0.1010*
Urinary Void Volume (mL)
Baseline | 175.0 (68.0) | 171.0 | 164.8 (62.3) | 160
Increase | 9.3 (63.1) | 5.5 | 32.0 (55.2) | 24
P value vs placebo | - |  | 0.0010*
*Comparison significant if p < 0.05

In a controlled clinical trial of skin sensitization, none of the 103 test subjects demonstrated skin hypersensitivity to OXYTROL.

Adhesion

Adhesion was periodically evaluated during the pivotal studies. Of the 4,746 OXYTROL evaluations in the trials, 20 (0.4%) were observed at clinic visits to have become completely detached and 35 (0.7%) became partially detached during routine clinic use. Similar to the pharmacokinetic studies, > 98% of the transdermal systems evaluated in the pivotal studies were assessed as being ≥ 75% attached and thus would be expected to perform as anticipated.

16 HOW SUPPLIED/STORAGE AND HANDLING

How Supplied

Unit Dose: Heat sealed pouch containing 1 OXYTROL (oxybutynin transdermal system).

Each 39 cm^2 transdermal system imprinted with “OXYTROL 3.9 mg/day” contains 36 mg of oxybutynin for nominal delivery of 3.9 mg oxybutynin per day when dosed in a twice weekly regimen.

Patient Calendar Box of 8 Transdermal Systems (NDC 0023-6153-08)

Storage

Store at 20-25°C (68-77°F). [See USP controlled room temperature.] Protect from moisture and humidity. Do not store outside the sealed pouch. Apply immediately after removal from the protective pouch. Discard used OXYTROL in household trash in a manner that prevents accidental application or ingestion by children, pets, or others.

Keep out of reach of children.

17 PATIENT COUNSELING INFORMATION

See FDA-Approved Patient Labeling (Patient Information and Instructions for Use)

Administration Instructions

Inform patients that OXYTROL should be applied to dry, intact skin on the abdomen, hip, or buttock and not be applied to areas that have been treated with oils, lotions or powders. OXYTROL should not be exposed to sunlight. Contact with water while bathing, swimming, showering or exercising will not change the effect of OXYTROL.

Do not divide or cut the transdermal system into pieces. Do not use if the transdermal system is damaged.

A new application site should be selected with each new transdermal system to avoid re-application to the same site within 7 days. Inform patients to try to change OXYTROL on the same 2 days each week and that the package of OXYTROL has a calendar checklist printed on the back to remind patients of their schedule. Inform patients to avoid rubbing the area of the transdermal system during bathing, swimming, showering or exercising. Inform patients that details on use of the transdermal system are explained in the Patient Information Leaflet.

Inform patients to discard used OXYTROL in household trash in a manner that prevents accidental application or ingestion by children, pets, or others. Inform patients to keep out of reach of children.

Important Anticholinergic Adverse Reactions

Inform patients that anticholinergic (antimuscarinic) agents, such as OXYTROL, may produce adverse reactions related to anticholinergic pharmacological activity including:

- Urinary retention and constipation.
- Heat prostration (due to decreased sweating) when anticholinergics such as OXYTROL are used in a hot environment.
- Dizziness or blurred vision. Patients should be advised to avoid driving or operating heavy machinery until OXYTROL’s effects have been determined.
- Drowsiness that may be worsened by alcohol.
- Angioedema has been reported with oral oxybutynin use. Patients should be advised to promptly discontinue OXYTROL and seek immediate medical attention if they experience symptoms consistent with angioedema.

Distributed By:
AbbVie, Inc.
North Chicago, IL 60064

© 2024 AbbVie. All rights reserved.

OXYTROL and its design are trademarks of Allergan Sales, LLC, an AbbVie company.

PATIENT INFORMATION
OXYTROL (OKSEE TROLE)
(oxybutynin transdermal system)

What is OXYTROL?
OXYTROL is a prescription medicine used to treat overactive bladder in men with symptoms of sudden need to urinate with leaking or wetting accidents (urge urinary incontinence), need to urinate right away (urgency), and a need to urinate often (frequency). OXYTROL is a transdermal system (patch) you apply to your skin.
It is not known if OXYTROL is safe and effective in children.

Do not use OXYTROL if:
• your bladder does not empty or does not empty completely when you urinate (urinary retention).
• your stomach empties slowly or incompletely after a meal (gastric retention).
• you have uncontrolled narrow-angle glaucoma (high pressure in your eye). Tell your doctor if you have glaucoma or a family history of glaucoma.
• you are allergic to oxybutynin or any of the ingredients in OXYTROL. See the end of this Patient Information leaflet for a complete list of ingredients in OXYTROL. If you have allergies to medical tape products or other skin patches, tell your doctor.

Before using OXYTROL, tell your doctor about all of your medical conditions, including if you:
• have problems emptying your bladder completely.
• have a gastrointestinal obstruction (blockage in the digestive system).
• have ulcerative colitis (inflamed bowels).
• have gastroesophageal reflux disease (GERD) or esophagitis (inflamed esophagus, the tube between your mouth and stomach).
• have myasthenia gravis (condition that causes muscle weakness).
Tell your doctor about all the medicines you take, including prescription and over-the-counter medicines, vitamins, and herbal supplements.
Using OXYTROL with certain other medicines may affect each other. Using OXYTROL with other medicines can cause serious side effects.
Especially tell your doctor if you take:
• medicines called “bisphosphonates” to treat osteoporosis
• medicines called “anticholinergics”
Ask your doctor or pharmacist for a list of these medicines if you are not sure you take any of these medicines.
Know the medicines you take. Keep a list of them and show it to your doctor and pharmacist when you get a new medicine.

How should I use OXYTROL?
• Read the Instructions for Use at the end of this Patient Information leaflet for information on the right way to use OXYTROL.
• Use OXYTROL exactly as your doctor tells you to use it.
• Put on a new patch of OXYTROL 2 times a week (every 3 to 4 days) according to your doctor’s instructions.
• Choose a new skin site for each new patch application. You should not use the same skin site within 7 days.
• Wear the patch all the time until it is time to apply a new one.
• Wear only 1 patch of OXYTROL at a time.
• Try to change the patch on the same 2 days each week.
• Your package of OXYTROL has a calendar checklist printed on the back to help you remember your schedule. Mark the schedule you plan to follow. Always change OXYTROL on the 2 days of the week you mark on the calendar.
• Contact with water when you are bathing, swimming, showering or exercising will not change the way that OXYTROL works.
• Do not divide or cut the patch into pieces. Damaged patches should not be used.

What should I avoid while using OXYTROL?
• You should not drink alcohol while using OXYTROL. Drinking alcohol can increase drowsiness that results from OXYTROL use.
• OXYTROL can cause dizziness or blurred vision. Do not drive, operate machinery, or do other dangerous activities until you know how OXYTROL affects you.
• Do not put OXYTROL on areas that have been treated with oils, lotions, or powders that could keep the patch from sticking well to your skin. Do not expose the patch to sunlight. Wear your patch under clothing.
• Avoid rubbing the patch area during bathing, swimming, showering or exercising.

What are the possible side effects of OXYTROL?
OXYTROL may cause serious side effects, including:
• inability to empty your bladder (urinary retention). OXYTROL may increase your chances of not being able to empty your bladder if you have a blockage at the base of your bladder that decreases or stops the flow of urine into the urethra, the tube that carries urine out of the body (bladder outlet obstruction). Tell your doctor right away if you are unable to empty your bladder.
• increased risk of stomach and esophagus problems in certain people. OXYTROL may cause stomach and esophagus problems in people who have a history of stomach or intestinal blockage, ulcerative colitis, intestinal atony, hiatal hernia, gastroesophageal reflux disease, or who are taking certain medicines called bisphosphonates.
• central nervous system effects. OXYTROL can cause central nervous system side effects including headache, dizziness, sleepiness, confusion, and seeing or hearing things that are not really there (hallucinations). Your doctor should monitor you for these effects after starting OXYTROL. See “What should I avoid while using OXYTROL.”
• swelling (angioedema). The active ingredient in OXYTROL, oxybutynin, can cause swelling around the eyes, lips, genitals, hands or feet. Some people who have taken oxybutynin medicines by mouth have had to be hospitalized. Stop using OXYTROL immediately and get emergency medical treatment right away if you have any of these symptoms.
• skin hypersensitivity. You may have skin changes where the patch was placed such as itching, rash, or redness. Tell your doctor if these changes do not go away or bother you.
• worsening of myasthenia gravis (condition that causes muscle weakness). OXYTROL may cause worsening of myasthenia gravis symptoms, including muscle weakness and breathing problems. Call your doctor right away if you have any worsening muscle weakness or breathing problems.
The most common side effects of OXYTROL include skin reactions where the patch is placed and dry mouth.
OXYTROL may cause you to sweat less and may increase your chances of being overheated, having a fever or heat stroke if you are in hot temperatures.
Tell your doctor if you have any side effect that bothers you or that does not go away or if you have constipation.
These are not all the possible side effects of OXYTROL. For a complete list, ask your doctor or pharmacist.
Call your doctor for medical advice about side effects. You may report side effects to FDA at 1-800-FDA- 1088.

How should I store OXYTROL?
• Store OXYTROL at room temperature between 68°F to 77°F (20°C to 25°C).
• Do not store OXYTROL outside the sealed pouch.
• Keep OXYTROL patches in a dry place.
• Safely throw away used OXYTROL patches in the household trash. Be careful to prevent accidental exposure of OXYTROL to children or pets.
Keep OXYTROL and all medicines out of the reach of children.

General information about the safe and effective use of OXYTROL.
Medicines are sometimes prescribed for purposes other than those listed in a Patient Information leaflet. Do not use OXYTROL for a condition for which it was not prescribed. Do not give OXYTROL to other people, even if they have the same symptoms you have. It may harm them. You can ask your pharmacist or doctor for information about OXYTROL that is written for health professionals.

What are the ingredients of OXYTROL?
Active Ingredient: oxybutynin
Inactive Ingredients: flexible polyester/ethylene-vinyl acetate film, acrylic adhesive, triacetin, siliconized polyester film.
For more information, go to www.OXYTROL.com or call 1-800-678-1605

Instructions for Use

OXYTROL (OKSEE TROLE)

(oxybutynin transdermal system)

Read this Instructions for Use that comes with your OXYTROL before you start using it and each time you get a refill. There may be new information. This information does not take the place of talking to your doctor about your medical condition or treatment.

Where to apply OXYTROL:

- Put the patch on a clean, dry, and smooth (fold-free) area of skin on your abdomen (stomach area), hips or buttocks. See Figure A.
- Avoid your waistline area, since tight clothing may rub against the patch.
- The areas you choose should not be oily, damaged (cut or scraped), irritated (rashes) or have any other skin problems.
- Do not put OXYTROL on areas that have been treated with oils, lotions, or powders that could keep the patch from sticking well to your skin.
- When you put on a new patch, use a different area of skin from the most recent patch site. You may find it useful to change the site from one side of your body to the other.
- Do not use the same area for the patch for at least 7 days. You may choose to try different sites when using OXYTROL to find the sites that are most comfortable for you and where clothing will not rub against it.
- Do not divide or cut the patch into pieces. Damaged patches should not be used.

How to apply OXYTROL:

Step 1.

- Each patch is sealed in its own protective pouch. See Figure B.
- When you are ready to put on your OXYTROL patch, tear open the pouch and remove the patch. See Figure C.

Step 2.

- The sticky adhesive side of the patch is covered by 2 strips of overlapping protective liner. See Figure D.
- Remove the first piece of the protective liner and place the patch, adhesive face down, firmly onto the skin. See Figure E.

Step 3.

- Bend the patch in half and gently roll the remaining part onto your skin using the tips of your fingers. As you roll the patch in place, the second piece of the protective liner should come off the patch. See Figure F.
- Apply firm pressure over the surface of the patch with your fingers to make sure the patch stays on. See Figure G.
- When putting on the patch, avoid touching the sticky adhesive side.
- Touching the adhesive may cause the patch to fall off early.
- Throw away the protective liners.
- If the patch partly or completely falls off, press it back in place and continue to follow your application schedule.
- If the patch does not stay on, throw it away. Put on a new patch on a different area of skin, and continue to follow your original application schedule.
- If you forget to change your patch after 3 or 4 days, remove the old patch, put on a new patch in a different area of skin and continue to follow your original application schedule.

How to remove OXYTROL:

- When changing your OXYTROL patch, remove the old patch slowly and carefully to avoid damaging your skin.
- After the old patch is removed, fold it in half with the sticky sides together.
- The patch will still contain some oxybutynin. Throw the patch away so that it cannot be worn or swallowed by another person, child, or pet.
- Gently wash the application site with warm water and a mild soap to remove any adhesive that stays on your skin after removing the patch.
- A small amount of baby oil may also be used to remove any adhesive remaining on your skin. Rings of adhesive that become dirty may need a medical adhesive removal pad that you can get from your pharmacist.
- Alcohol or other dissolving liquids (nail polish remover or other solvents) may cause skin irritation and should not be used.

This Patient Information and Instructions for Use has been approved by the U.S. Food and Drug Administration.

Distributed By:
AbbVie, Inc.
North Chicago, IL 60064

© 2024 AbbVie. All rights reserved.

OXYTROL and its design are trademarks of Allergan Sales, LLC, an AbbVie company.

Revised: 05/2024

PRINCIPAL DISPLAY PANEL

NDC 0023-6153-08
OXYTROL®
Oxybutynin Transdermal System
3.9 mg/day
Nominal delivery of 3.9 mg/day.
Continuous delivery for twice weekly dosing.
Each 39 cm^2 system contains 36 mg oxybutynin.
Inactive Components: triacetin, USP; acrylic adhesive;
polyester/ethylene-vinyl acetate film, and siliconized polyester film.
Contains 8 transdermal systems
Keep out of reach of children.
Do not divide or cut the transdermal system into pieces. Do not use
If the transdermal system is damaged, cut, or altered in any way.
Rx only
abbvie